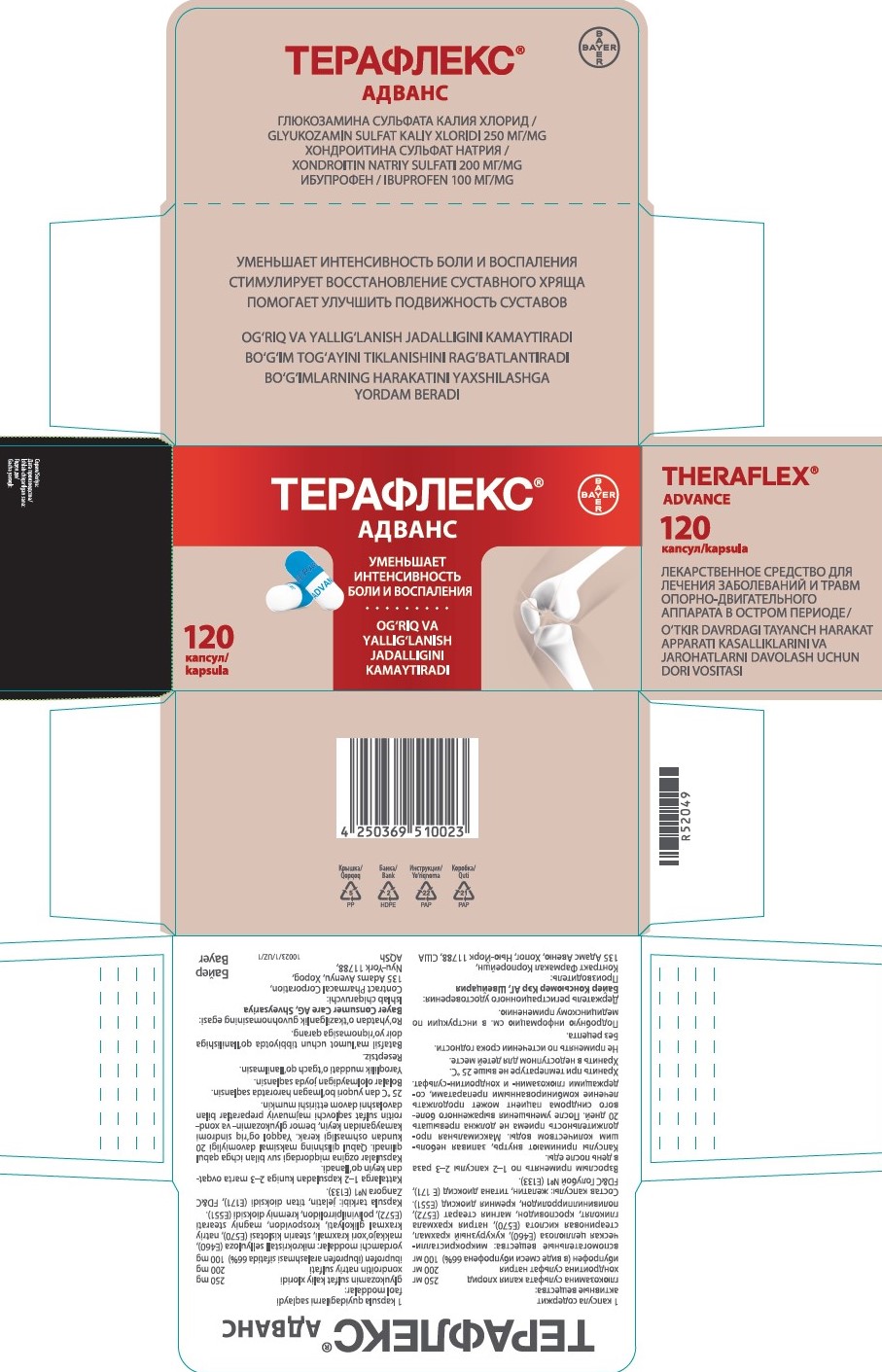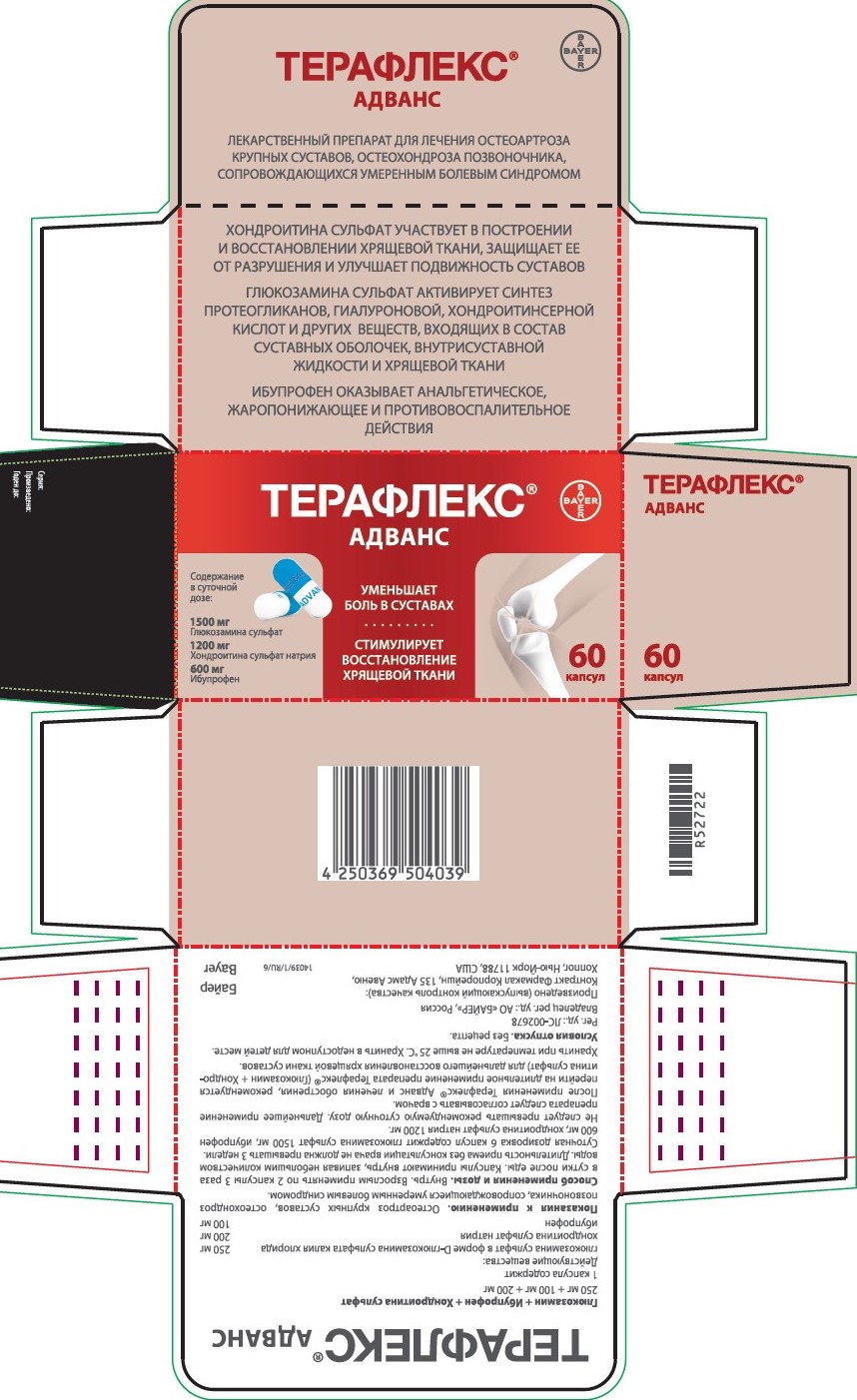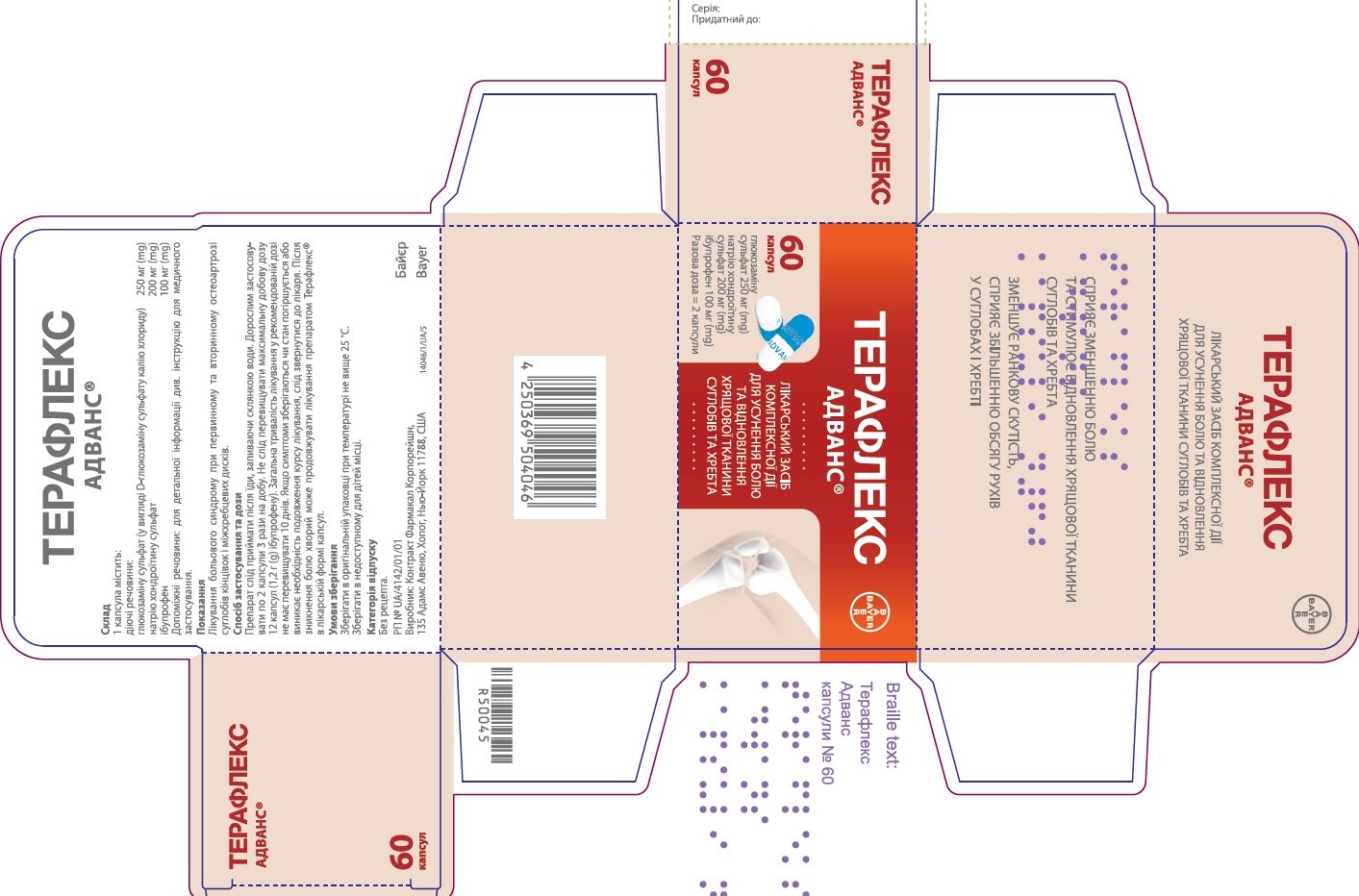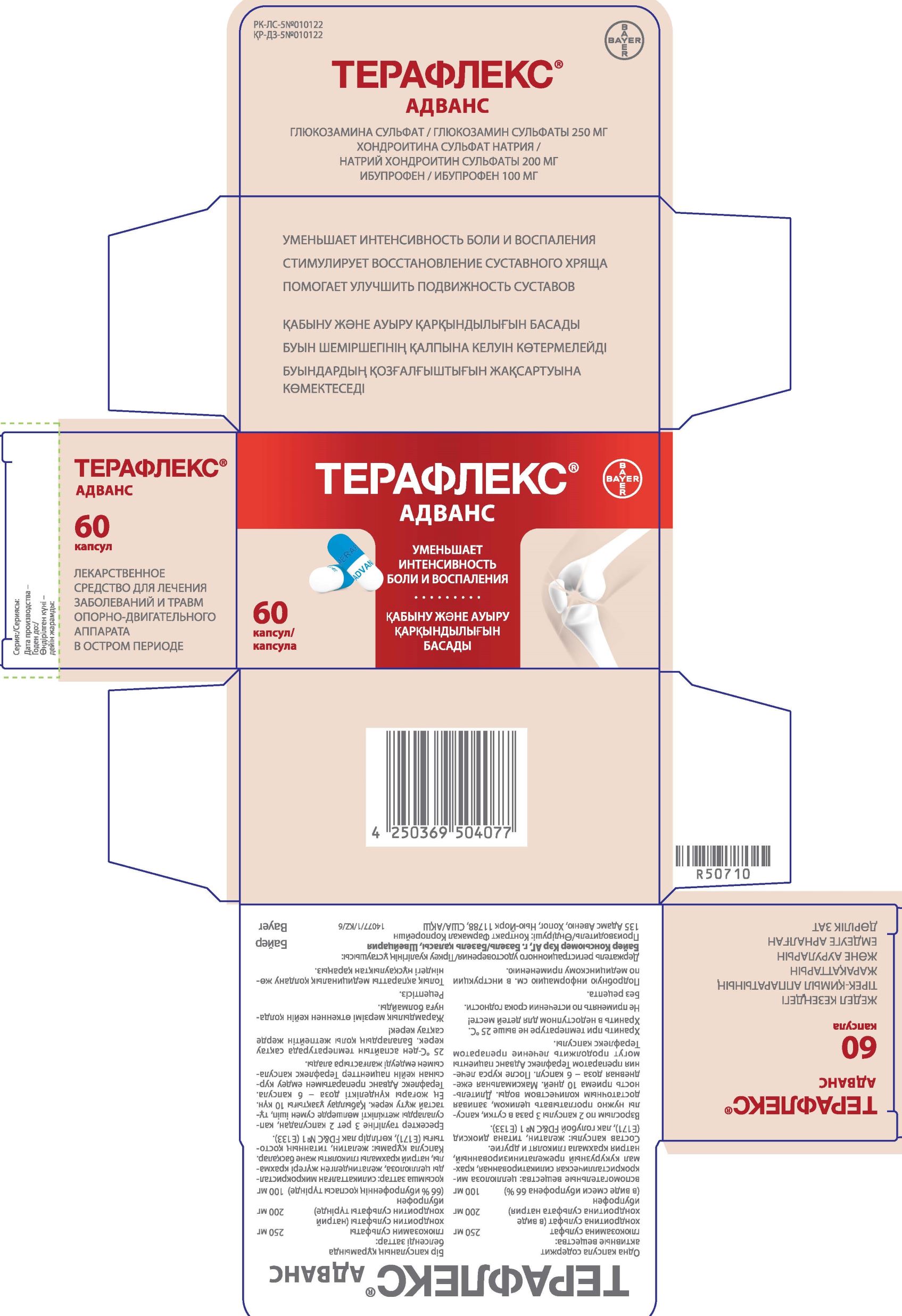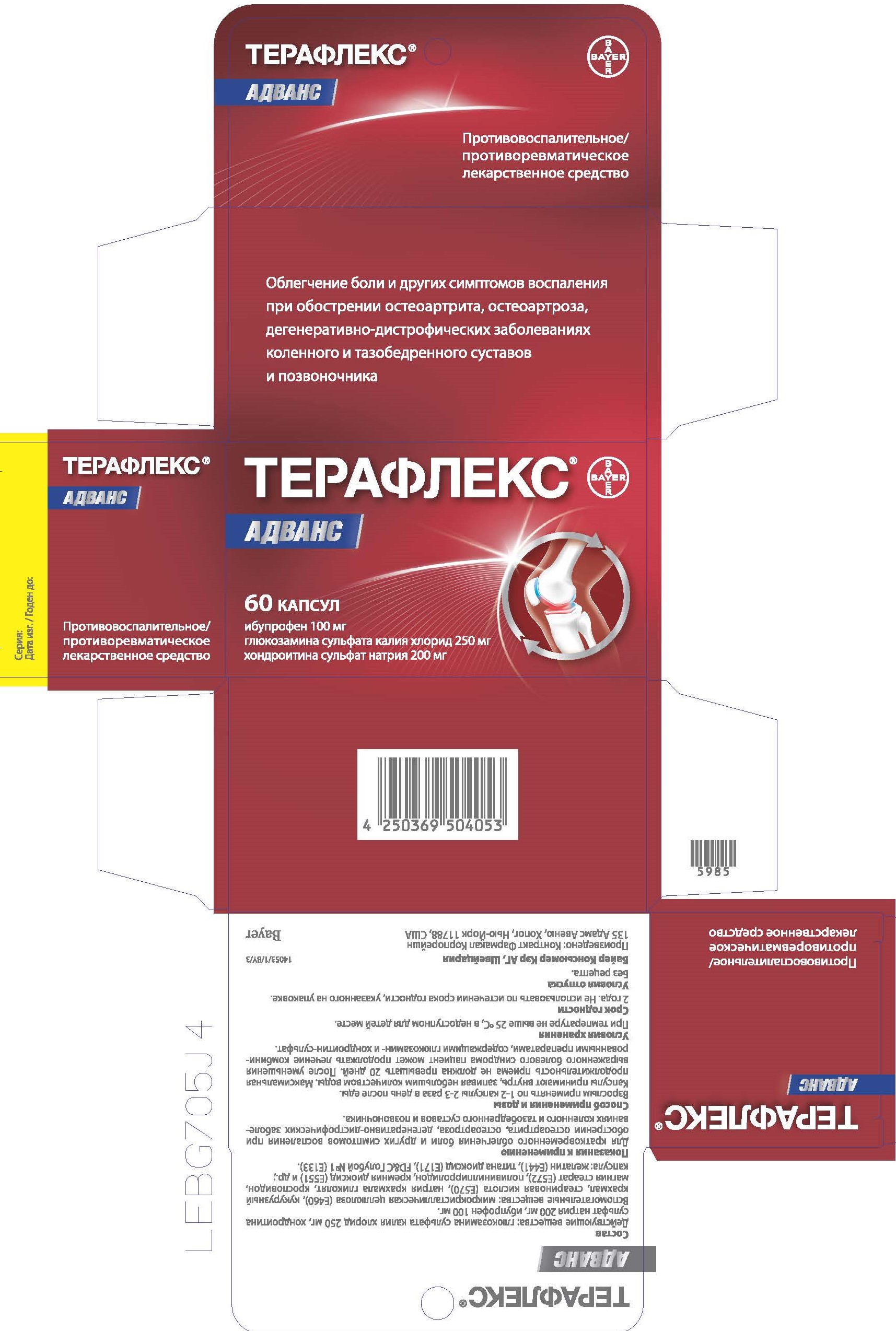 DRUG LABEL: Glucosamine Sulfate, Chondroitin Sulfate, Ibuprofen
NDC: 10267-3479 | Form: CAPSULE
Manufacturer: Contract Pharmacal Corp.
Category: otc | Type: HUMAN OTC DRUG LABEL
Date: 20250630

ACTIVE INGREDIENTS: CHONDROITIN SULFATE (BOVINE) 200 mg/1 1; GLUCOSAMINE SULFATE 250 mg/1 1; IBUPROFEN 100 mg/1 1
INACTIVE INGREDIENTS: STARCH, CORN; CROSPOVIDONE; STEARIC ACID; FD&C BLUE NO. 1; MICROCRYSTALLINE CELLULOSE; MAGNESIUM STEARATE; GELATIN; SILICON DIOXIDE; TITANIUM DIOXIDE; SODIUM STARCH GLYCOLATE TYPE A POTATO; POVIDONE K30; CROSCARMELLOSE SODIUM

3479- Export